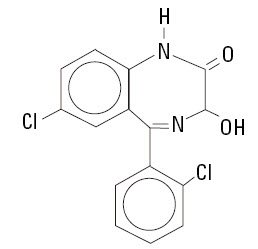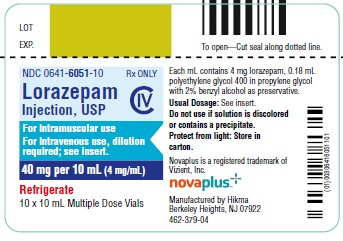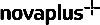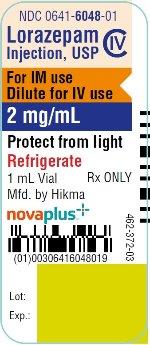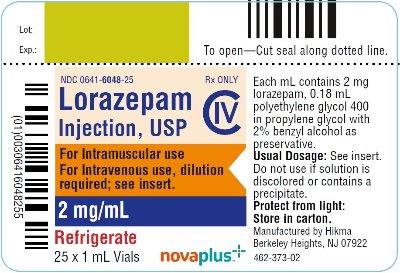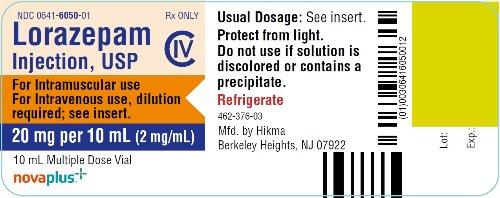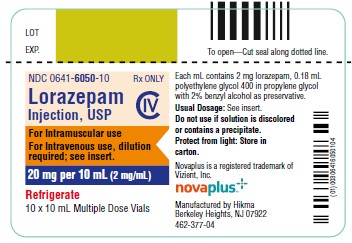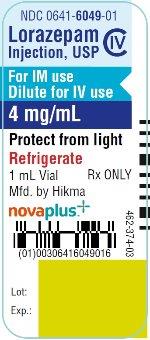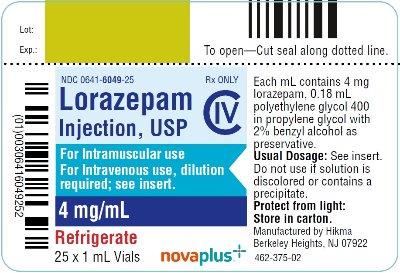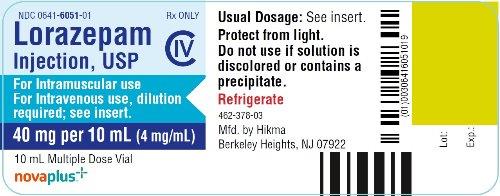 DRUG LABEL: Lorazepam
NDC: 0641-6048 | Form: INJECTION
Manufacturer: Hikma Pharmaceuticals USA Inc.
Category: prescription | Type: HUMAN PRESCRIPTION DRUG LABEL
Date: 20240410
DEA Schedule: CIV

ACTIVE INGREDIENTS: LORAZEPAM 2.0 mg/1 mL
INACTIVE INGREDIENTS: POLYETHYLENE GLYCOL 400 0.18 mL/1 mL; BENZYL ALCOHOL; PROPYLENE GLYCOL

Lorazepam Injection, USP

CIV

For intravenous and intramuscular use

NOT FOR USE IN NEONATES

CONTAINS BENZYL ALCOHOL

BOXED WARNING

WARNING: RISKS FROM CONCOMITANT USE WITH OPIOIDS; ABUSE, MISUSE, AND ADDICTION; and DEPENDENCE AND WITHDRAWAL REACTIONS

- Concomitant use of benzodiazepines and opioids may result in profound sedation, respiratory depression, coma, and death. Reserve concomitant prescribing of these drugs in patients for whom alternative treatment options are inadequate. Limit dosages and durations to the minimum required. Follow patients for signs and symptoms of respiratory depression and sedation (see WARNINGS and PRECAUTIONS).
- The use of benzodiazepines, including Lorazepam Injection, exposes users to risks of abuse, misuse, and addiction, which can lead to overdose or death. Abuse and misuse of benzodiazepines commonly involve concomitant use of other medications, alcohol, and/or illicit substances, which is associated with an increased frequency of serious adverse outcomes. Before prescribing Lorazepam Injection and throughout treatment, assess each patient’s risk for abuse, misuse, and addiction (see WARNINGS).
- The continued use of benzodiazepines for several days to weeks may lead to clinically significant physical dependence. The risks of dependence and withdrawal increase with longer treatment duration and higher daily dose. Although Lorazepam Injection is indicated only for intermittent use (see INDICATIONS AND USAGE and DOSAGE AND ADMINISTRATION), if used more frequently than recommended, abrupt discontinuation or rapid dosage reduction of Lorazepam Injection may precipitate acute withdrawal reactions, which can be life-threatening. For patients using Lorazepam Injection more frequently than recommended, to reduce the risk of withdrawal reactions, use a gradual taper to discontinue Lorazepam Injection (see WARNINGS).

DESCRIPTION

Lorazepam, a benzodiazepine with antianxiety, sedative, and anticonvulsant effects, is intended for the intramuscular or intravenous routes of administration. It has the chemical formula: 7-chloro-5(2-chlorophenyl)-1,3-dihydro-3-hydroxy-2H-1,4-benzodiazepin-2-one. The molecular weight is 321.16, and the C.A.S. No. is [846-49-1]. The structural formula is:

Lorazepam is a nearly white powder almost insoluble in water. Each mL of sterile injection contains either 2.0 or 4.0 mg of lorazepam, 0.18 mL polyethylene glycol 400 in propylene glycol with 2.0% benzyl alcohol as preservative.

CLINICAL PHARMACOLOGY

Lorazepam interacts with the γ-aminobutyric acid (GABA)-benzodiazepine receptor complex, which is widespread in the brain of humans as well as other species. This interaction is presumed to be responsible for lorazepam’s mechanism of action. Lorazepam exhibits relatively high and specific affinity for its recognition site but does not displace GABA. Attachment to the specific binding site enhances the affinity of GABA for its receptor site on the same receptor complex. The pharmacodynamic consequences of benzodiazepine agonist actions include antianxiety effects, sedation, and reduction of seizure activity. The intensity of action is directly related to the degree of benzodiazepine receptor occupancy.

Effects in Pre-Operative Patients

Intravenous or intramuscular administration of the recommended dose of 2 mg to 4 mg of Lorazepam Injection to adult patients is followed by dose-related effects of sedation (sleepiness or drowsiness), relief of preoperative anxiety, and lack of recall of events related to the day of surgery in the majority of patients. The clinical sedation (sleepiness or drowsiness) thus noted is such that the majority of patients are able to respond to simple instructions whether they give the appearance of being awake or asleep. The lack of recall is relative rather than absolute, as determined under conditions of careful patient questioning and testing, using props designed to enhance recall. The majority of patients under these reinforced conditions had difficulty recalling perioperative events or recognizing props from before surgery. The lack of recall and recognition was optimum within 2 hours following intramuscular administration and 15 to 20 minutes after intravenous injection.

The intended effects of the recommended adult dose of Lorazepam Injection usually last 6 to 8 hours. In rare instances, and where patients received greater than the recommended dose, excessive sleepiness and prolonged lack of recall were noted. As with other benzodiazepines, unsteadiness, enhanced sensitivity to CNS-depressant effects of ethyl alcohol and other drugs were noted in isolated and rare cases for greater than 24 hours.

Physiologic Effects in Healthy Adults

Studies in healthy adult volunteers reveal that intravenous lorazepam in doses up to 3.5 mg/70 kg does not alter sensitivity to the respiratory stimulating effect of carbon dioxide and does not enhance the respiratory-depressant effects of doses of meperidine up to 100 mg/70 kg (also determined by carbon dioxide challenge) as long as patients remain sufficiently awake to undergo testing. Upper airway obstruction has been observed in rare instances where the patient received greater than the recommended dose and was excessively sleepy and difficult to arouse (see WARNINGS and ADVERSE REACTIONS).

Clinically employed doses of Lorazepam Injection do not greatly affect the circulatory system in the supine position or employing a 70-degree tilt test. Doses of 8 mg to 10 mg of intravenous lorazepam (2 to 2-1/2 times the maximum recommended dosage) will produce loss of lid reflexes within 15 minutes.

Studies in 6 healthy young adults who received Lorazepam Injection and no other drugs revealed that visual tracking (the ability to keep a moving line centered) was impaired for a mean of 8 hours following administration of 4 mg of intramuscular lorazepam and 4 hours following administration of 2 mg intramuscularly with considerable subject variation. Similar findings were noted with pentobarbital, 150 and 75 mg. Although this study showed that both lorazepam and pentobarbital interfered with eye-hand coordination, the data are insufficient to predict when it would be safe to operate a motor vehicle or engage in a hazardous occupation or sport.

Pharmacokinetics and Metabolism

ABSORPTION

Intravenous

A 4-mg dose provides an initial concentration of approximately 70 ng/mL.

Intramuscular

Following intramuscular administration, lorazepam is completely and rapidly absorbed reaching peak concentrations within 3 hours. A 4-mg dose provides a Cmax of approximately 48 ng/mL. Following administration of 1.5 to 5.0 mg of lorazepam IM, the amount of lorazepam delivered to the circulation is proportional to the dose administered.

DISTRIBUTION/METABOLISM/ELIMINATION

At clinically relevant concentrations, lorazepam is 91±2% bound to plasma proteins; its volume of distribution is approximately 1.3 L/kg. Unbound lorazepam penetrates the blood/brain barrier freely by passive diffusion, a fact confirmed by CSF sampling. Following parenteral administration, the terminal half-life and total clearance averaged 14±5 hours and 1.1±0.4 mL/min/kg, respectively.

Lorazepam is extensively conjugated to the 3-O-phenolic glucuronide in the liver and is known to undergo enterohepatic recirculation. Lorazepam glucuronide is an inactive metabolite and is eliminated mainly by the kidneys.

Following a single 2-mg oral dose of ^14C-lorazepam to 8 healthy subjects, 88±4% of the administered dose was recovered in urine and 7±2% was recovered in feces. The percent of administered dose recovered in urine as lorazepam glucuronide was 74±4%. Only 0.3% of the dose was recovered as unchanged lorazepam, and the remainder of the radioactivity represented minor metabolites.

Special Populations

EFFECT OF AGE

Pediatrics

NEONATES (BIRTH TO 1 MONTH)

Following a single 0.05 mg/kg (n=4) or 0.1 mg/kg (n=6) intravenous dose of lorazepam, mean total clearance normalized to body weight was reduced by 80% compared to normal adults, terminal half-life was prolonged 3-fold, and volume of distribution was decreased by 40% in neonates with asphyxia neonatorum compared to normal adults. All neonates were of ≥37 weeks of gestational age.

INFANTS (1 MONTH UP TO 2 YEARS)

There is no information on the pharmacokinetic profile of lorazepam in infants in the age range of 1 month to 2 years.

CHILDREN (2 YEARS TO 12 YEARS)

Total (bound and unbound) lorazepam had a 50% higher mean volume of distribution (normalized to body-weight) and a 30% longer mean half-life in children with acute lymphocytic leukemia in complete remission (2 to 12 years, n=37) compared to normal adults (n=10). Unbound lorazepam clearance normalized to body-weight was comparable in children and adults.

ADOLESCENTS (12 YEARS TO 18 YEARS)

Total (bound and unbound) lorazepam had a 50% higher mean volume of distribution (normalized to body-weight) and a mean half-life that was two fold greater in adolescents with acute lymphocytic leukemia in complete remission (12 to 18 years, n=13) compared to normal adults (n=10). Unbound lorazepam clearance normalized to body-weight was comparable in adolescents and adults.

Elderly

Following single intravenous doses of 1.5 to 3 mg of Lorazepam Injection, mean total body clearance of lorazepam decreased by 20% in 15 elderly subjects of 60 to 84 years of age compared to that in 15 younger subjects of 19 to 38 years of age. Consequently, no dosage adjustment appears to be necessary in elderly subjects based solely on their age.

EFFECT OF GENDER

Gender has no effect on the pharmacokinetics of lorazepam.

EFFECT OF RACE

Young Americans (n=15) and Japanese subjects (n=7) had very comparable mean total clearance value of 1.0 mL/min/kg. However, elderly Japanese subjects had a 20% lower mean total clearance than elderly Americans, 0.59 mL/min/kg vs 0.77 mL/min/kg, respectively.

PATIENTS WITH RENAL INSUFFICIENCY

Because the kidney is the primary route of elimination of lorazepam glucuronide, renal impairment would be expected to compromise its clearance. This should have no direct effect on the glucuronidation (and inactivation) of lorazepam. There is a possibility that the enterohepatic circulation of lorazepam glucuronide leads to a reduced efficiency of the net clearance of lorazepam in this population.

Six normal subjects, six patients with renal impairment (Clcr of 22±9 mL/min), and four patients on chronic maintenance hemodialysis were given single 1.5 to 3.0 mg intravenous doses of lorazepam. Mean volume of distribution and terminal half-life values of lorazepam were 40% and 25% higher, respectively, in renally impaired patients than in normal subjects. Both parameters were 75% higher in patients undergoing hemodialysis than in normal subjects. Overall, though, in this group of subjects the mean total clearance of lorazepam did not change. About 8% of the administered intravenous dose was removed as intact lorazepam during the 6-hour dialysis session.

The kinetics of lorazepam glucuronide were markedly affected by renal dysfunction. The mean terminal half-life was prolonged by 55% and 125% in renally impaired patients and patients under hemodialysis, respectively, as compared to normal subjects. The mean metabolic clearance decreased by 75% and 90% in renally impaired patients and patients under hemodialysis, respectively, as compared with normal subjects. About 40% of the administered lorazepam intravenous dose was removed as glucuronide conjugate during the 6-hour dialysis session.

HEPATIC DISEASE

Because cytochrome oxidation is not involved with the metabolism of lorazepam, liver disease would not be expected to have an effect on metabolic clearance. This prediction is supported by the observation that following a single 2 mg intravenous dose of lorazepam, cirrhotic male patients (n=13) and normal male subjects (n=11) exhibited no substantive difference in their ability to clear lorazepam.

EFFECT OF SMOKING

Administration of a single 2 mg intravenous dose of lorazepam showed that there was no difference in any of the pharmacokinetic parameters of lorazepam between cigarette smokers (n=10, mean=31 cigarettes per day) and nonsmoking subjects (n=10) who were matched for age, weight and gender.

Clinical Studies

The effectiveness of Lorazepam Injection in status epilepticus was established in two multi-center controlled trials in 177 patients. With rare exceptions, patients were between 18 and 65 years of age. More than half the patients in each study had tonic-clonic status epilepticus; patients with simple partial and complex partial status epilepticus comprised the rest of the population studied, along with a smaller number of patients who had absence status.

One study (n=58) was a double-blind active-control trial comparing Lorazepam Injection and diazepam. Patients were randomized to receive lorazepam 2 mg IV (with an additional 2 mg IV if needed) or diazepam 5 mg IV (with an additional 5 mg IV if needed). The primary outcome measure was a comparison of the proportion of responders in each treatment group, where a responder was defined as a patient whose seizures stopped within 10 minutes after treatment and who continued seizure-free for at least an additional 30 minutes. Twenty-four of the 30 (80%) patients were deemed responders to lorazepam and 16/28 (57%) patients were deemed responders to diazepam (p=0.04). Of the 24 lorazepam responders, 23 received both 2 mg infusions.

Non-responders to lorazepam 4 mg were given an additional 2 to 4 mg lorazepam; non-responders to diazepam 10 mg were given an additional 5 to 10 mg diazepam. After this additional dose administration, 28/30 (93%) of patients randomized to lorazepam and 24/28 (86%) of patients randomized to diazepam were deemed responders, a difference that was not statistically significant.

Although this study provides support for the efficacy of lorazepam as the treatment for status epilepticus, it cannot speak reliably or meaningfully to the comparative performance of either diazepam (Valium) or lorazepam (Lorazepam Injection) under the conditions of actual use.

A second study (n=119) was a double-blind dose-comparison trial with 3 doses of Lorazepam Injection: 1 mg, 2 mg, and 4 mg. Patients were randomized to receive one of the three doses of lorazepam. The primary outcome and definition of responder were as in the first study. Twenty-five of 41 patients (61%) responded to 1 mg lorazepam; 21/37 patients (57%) responded to 2 mg lorazepam; and 31/41 (76%) responded to 4 mg lorazepam. The p-value for a statistical test of the difference between the lorazepam 4 mg dose group and the lorazepam 1 mg dose group was 0.08 (two-sided). Data from all randomized patients were used in this test.

Although analyses failed to detect an effect of age, sex, or race on the effectiveness of lorazepam in status epilepticus, the numbers of patients evaluated were too few to allow a definitive conclusion about the role these factors may play.

INDICATIONS AND USAGE

Status Epilepticus

Lorazepam Injection is indicated for the treatment of status epilepticus.

Preanesthetic

Lorazepam Injection is indicated in adult patients for preanesthetic medication, producing sedation (sleepiness or drowsiness), relief of anxiety, and a decreased ability to recall events related to the day of surgery. It is most useful in those patients who are anxious about their surgical procedure and who would prefer to have diminished recall of the events of the day of surgery (see PRECAUTIONS, Information for Patients).

CONTRAINDICATIONS

Lorazepam Injection is contraindicated in patients with a known sensitivity to benzodiazepines or its vehicle (polyethylene glycol, propylene glycol, and benzyl alcohol), in patients with acute narrow-angle glaucoma, or in patients with sleep apnea syndrome. It is also contraindicated in patients with severe respiratory insufficiency, except in those patients requiring relief of anxiety and/or diminished recall of events while being mechanically ventilated. The use of Lorazepam Injection intra-arterially is contraindicated because, as with other injectable benzodiazepines, inadvertent intra-arterial injection may produce arteriospasm resulting in gangrene which may require amputation (see WARNINGS).

Lorazepam Injection is contraindicated for use in premature infants because the formulation contains benzyl alcohol (see WARNINGS and PRECAUTIONS, Pediatric Use).

WARNINGS

Risks from Concomitant Use with Opioids

Concomitant use of benzodiazepines, including Lorazepam Injection, and opioids may result in profound sedation, respiratory depression, coma, and death. If a decision is made to use Lorazepam Injection concomitantly with opioids, monitor patients closely for respiratory depression and sedation (see PRECAUTIONS, Drug Interactions).

Abuse, Misuse, and Addiction

The use of benzodiazepines, including Lorazepam Injection, exposes users to the risks of abuse, misuse, and addiction, which can lead to overdose or death. Abuse and misuse of benzodiazepines often (but not always) involve the use of doses greater than the maximum recommended dosage and commonly involve concomitant use of other medications, alcohol, and/or illicit substances, which is associated with an increased frequency of serious adverse outcomes, including respiratory depression, overdose, or death (see DRUG ABUSE AND DEPENDENCE, Abuse).

Before prescribing Lorazepam Injection and throughout treatment, assess each patient’s risk for abuse, misuse, and addiction. Use of Lorazepam Injection, particularly in patients at elevated risk, necessitates counseling about the risks and proper use of Lorazepam Injection along with monitoring for signs and symptoms of abuse, misuse, and addiction. Do not exceed the recommended dosing frequency; avoid or minimize concomitant use of CNS depressants and other substances associated with abuse, misuse, and addiction (e.g., opioid analgesics, stimulants); and advise patients on the proper disposal of unused drug. If a substance use disorder is suspected, evaluate the patient and institute (or refer them for) early treatment, as appropriate.

Dependence and Withdrawal Reactions After Use of Lorazepam Injection More Frequently Than Recommended

For patients using Lorazepam Injection more frequently than recommended, to reduce the risk of withdrawal reactions, use a gradual taper to discontinue Lorazepam Injection (a patient-specific plan should be used to taper the dose).
Patients at an increased risk of withdrawal adverse reactions after benzodiazepine discontinuation or rapid dosage reduction include those who take higher dosages, and those who have had longer durations of use.
ACUTE WITHDRAWAL REACTIONS
The continued use of benzodiazepines may lead to clinically significant physical dependence. Although Lorazepam Injection is indicated only for intermittent use (see INDICATIONS AND USAGE and DOSAGE AND ADMINISTRATION), if used more frequently than recommended, abrupt discontinuation or rapid dosage reduction of Lorazepam Injection, or administration of flumazenil (a benzodiazepine antagonist) may precipitate acute withdrawal reactions, which can be life-threatening (e.g., seizures) (see DRUG ABUSE AND DEPENDENCE, Dependence).
PROTRACTED WITHDRAWAL SYNDROME
In some cases, benzodiazepine users have developed a protracted withdrawal syndrome with withdrawal symptoms lasting weeks to more than 12 months (see DRUG ABUSE AND DEPENDENCE, Dependence).

Use in Status Epilepticus

MANAGEMENT OF STATUS EPILEPTICUS

Status epilepticus is a potentially life-threatening condition associated with a high risk of permanent neurological impairment, if inadequately treated. The treatment of status, however, requires far more than the administration of an anticonvulsant agent. It involves observation and management of all parameters critical to maintaining vital function and the capacity to provide support of those functions as required. Ventilatory support must be readily available. The use of benzodiazepines, like Lorazepam Injection, is ordinarily only one step of a complex and sustained intervention which may require additional interventions (e.g., concomitant intravenous administration of phenytoin). Because status epilepticus may result from a correctable acute cause such as hypoglycemia, hyponatremia, or other metabolic or toxic derangement, such an abnormality must be immediately sought and corrected. Furthermore, patients who are susceptible to further seizure episodes should receive adequate maintenance antiepileptic therapy.

Any healthcare professional who intends to treat a patient with status epilepticus should be familiar with this package insert and the pertinent medical literature concerning current concepts for the treatment of status epilepticus. A comprehensive review of the considerations critical to the informed and prudent management of status epilepticus cannot be provided in drug product labeling. The archival medical literature contains many informative references on the management of status epilepticus, among them the report of the working group on status epilepticus of the Epilepsy Foundation of America “Treatment of Convulsive Status Epilepticus” (JAMA 1993; 270:854-859). As noted in the report just cited, it may be useful to consult with a neurologist if a patient fails to respond (e.g., fails to regain consciousness).

For the treatment of status epilepticus, the usual recommended dose of Lorazepam Injection is 4 mg given slowly (2 mg/min) for patients 18 years and older. If seizures cease, no additional Lorazepam Injection is required. If seizures continue or recur after a 10- to 15-minute observation period, an additional 4 mg intravenous dose may be slowly administered. Experience with further doses of lorazepam is very limited. The usual precautions in treating status epilepticus should be employed. An intravenous infusion should be started, vital signs should be monitored, an unobstructed airway should be maintained, and artificial ventilation equipment should be available.

RESPIRATORY DEPRESSION

The most important risk associated with the use of Lorazepam Injection in status epilepticus is respiratory depression. Accordingly, airway patency must be assured and respiration monitored closely. Ventilatory support should be given as required.

EXCESSIVE SEDATION

Because of its prolonged duration of action, the prescriber should be alert to the possibility, especially when multiple doses have been given, that the sedative effects of lorazepam may add to the impairment of consciousness seen in the post-ictal state.

Preanesthetic Use

AIRWAY OBSTRUCTION MAY OCCUR IN HEAVILY SEDATED PATIENTS. INTRAVENOUS LORAZEPAM AT ANY DOSE, WHEN GIVEN EITHER ALONE OR IN COMBINATION WITH OTHER DRUGS ADMINISTERED DURING ANESTHESIA, MAY PRODUCE HEAVY SEDATION; THEREFORE, EQUIPMENT NECESSARY TO MAINTAIN A PATENT AIRWAY AND TO SUPPORT RESPIRATION/VENTILATION SHOULD BE AVAILABLE.

As is true of similar CNS-acting drugs, the decision as to when patients who have received injectable lorazepam, particularly on an outpatient basis, may again operate machinery, drive a motor vehicle, or engage in hazardous or other activities requiring attention and coordination must be individualized. It is recommended that no patient engage in such activities for a period of 24 to 48 hours or until the effects of the drug, such as drowsiness, have subsided, whichever is longer. Impairment of performance may persist for greater intervals because of extremes of age, concomitant use of other drugs, stress of surgery, or the general condition of the patient.

Clinical trials have shown that patients over the age of 50 years may have a more profound and prolonged sedation with intravenous lorazepam (see DOSAGE AND ADMINISTRATION, Preanesthetic).

As with all central-nervous-system-depressant drugs, care should be exercised in patients given injectable lorazepam as premature ambulation may result in injury from falling.

There is no added beneficial effect from the addition of scopolamine to injectable lorazepam, and their combined effect may result in an increased incidence of sedation, hallucination and irrational behavior.

General (All Uses)

PRIOR TO INTRAVENOUS USE, LORAZEPAM INJECTION MUST BE DILUTED WITH AN EQUAL AMOUNT OF COMPATIBLE DILUENT (see DOSAGE AND ADMINISTRATION). INTRAVENOUS INJECTION SHOULD BE MADE SLOWLY AND WITH REPEATED ASPIRATION. CARE SHOULD BE TAKEN TO DETERMINE THAT ANY INJECTION WILL NOT BE INTRA-ARTERIAL AND THAT PERIVASCULAR EXTRAVASATION WILL NOT TAKE PLACE. IN THE EVENT THAT A PATIENT COMPLAINS OF PAIN DURING INTENDED INTRAVENOUS INJECTION OF LORAZEPAM INJECTION, THE INJECTION SHOULD BE STOPPED IMMEDIATELY TO DETERMINE IF INTRA-ARTERIAL INJECTION OR PERIVASCULAR EXTRAVASATION HAS TAKEN PLACE.

Since the liver is the most likely site of conjugation of lorazepam and since excretion of conjugated lorazepam (glucuronide) is a renal function, this drug is not recommended for use in patients with hepatic and/or renal failure. Lorazepam should be used with caution in patients with mild-to-moderate hepatic or renal disease (see DOSAGE AND ADMINISTRATION).

Pregnancy

LORAZEPAM MAY CAUSE FETAL DAMAGE WHEN ADMINISTERED TO PREGNANT WOMEN. Ordinarily, Lorazepam Injection should not be used during pregnancy except in serious or life-threatening conditions where safer drugs cannot be used or are ineffective. Status epilepticus may represent such a serious and life-threatening condition.

An increased risk of congenital malformations associated with the use of minor tranquilizers (chlordiazepoxide, diazepam and meprobamate) during the first trimester of pregnancy has been suggested in several studies. In humans, blood levels obtained from umbilical cord blood indicate placental transfer of lorazepam and lorazepam glucuronide.

Reproductive studies in animals were performed in mice, rats, and two strains of rabbits. Occasional anomalies (reduction of tarsals, tibia, metatarsals, malrotated limbs, gastroschisis, malformed skull, and microphthalmia) were seen in drug-treated rabbits without relationship to dosage. Although all of these anomalies were not present in the concurrent control group, they have been reported to occur randomly in historical controls. At doses of 40 mg/kg orally or 4 mg/kg intravenously and higher, there was evidence of fetal resorption and increased fetal loss in rabbits which was not seen at lower doses.

The possibility that a woman of childbearing potential may be pregnant at the time of therapy should be considered.

There are insufficient data regarding obstetrical safety of parenteral lorazepam, including use in cesarean section. Such use, therefore, is not recommended.

Usage in Preterm Infants and Neonates

Lorazepam Injection contains benzyl alcohol. Exposure to excessive amounts of benzyl alcohol has been associated with toxicity (hypotension, metabolic acidosis), particularly in neonates, and an increased incidence of kernicterus, particularly in small preterm infants. There have been rare reports of deaths, primarily in preterm infants, associated with exposure to excessive amounts of benzyl alcohol. The amount of benzyl alcohol from medications is usually considered negligible compared to that received in flush solutions containing benzyl alcohol. Administration of high dosages of medications (including lorazepam) containing this preservative must take into account the total amount of benzyl alcohol administered. The recommended dosage range of lorazepam for preterm and term infants includes amounts of benzyl alcohol well below that associated with toxicity; however, the amount of benzyl alcohol at which toxicity may occur is not known. If the patient requires more than the recommended dosages or other medications containing this preservative, the practitioner must consider the daily metabolic load of benzyl alcohol from these combined sources (see WARNINGS and PRECAUTIONS, Pediatric Use).

Pediatric Neurotoxicity

Published animal studies demonstrate that the administration of anesthetic and sedation drugs that block NMDA receptors and/or potentiate GABA activity increase neuronal apoptosis in the developing brain and result in long-term cognitive deficits when used for longer than 3 hours. The clinical significance of these findings is not clear. However, based on the available data, the window of vulnerability to these changes is believed to correlate with exposures in the third trimester of gestation through the first several months of life, but may extend out to approximately three years of age in humans (see PRECAUTIONS, Pregnancy, Pediatric Use; ANIMAL TOXICOLOGY AND/OR PHARMACOLOGY).

Some published studies in children suggest that similar deficits may occur after repeated or prolonged exposures to anesthetic agents early in life and may result in adverse cognitive or behavioral effects. These studies have substantial limitations, and it is not clear if the observed effects are due to the anesthetic/sedation drug administration or other factors such as the surgery or underlying illness.

Anesthetic and sedation drugs are a necessary part of the care of children needing surgery, other procedures, or tests that cannot be delayed, and no specific medications have been shown to be safer than any other. Decisions regarding the timing of any elective procedures requiring anesthesia should take into consideration the benefits of the procedure weighed against the potential risks.

Endoscopic Procedures

There are insufficient data to support the use of Lorazepam Injection for outpatient endoscopic procedures. Inpatient endoscopic procedures require adequate recovery room observation time.

When Lorazepam Injection is used for peroral endoscopic procedures, adequate topical or regional anesthesia is recommended to minimize reflex activity associated with such procedures.

PRECAUTIONS

General

The additive central-nervous-system effects of other drugs, such as phenothiazines, narcotic analgesics, barbiturates, antidepressants, scopolamine, and monoamine-oxidase inhibitors, should be borne in mind when these other drugs are used concomitantly with or during the period of recovery from Lorazepam Injection (see CLINICAL PHARMACOLOGY and WARNINGS).

Extreme caution must be used when administering Lorazepam Injection to elderly patients, very ill patients, or to patients with limited pulmonary reserve because of the possibility that hypoventilation and/or hypoxic cardiac arrest may occur. Resuscitative equipment for ventilatory support should be readily available (see WARNINGS and DOSAGE AND ADMINISTRATION).

When lorazepam injection is used IV as the premedicant prior to regional or local anesthesia, the possibility of excessive sleepiness or drowsiness may interfere with patient cooperation in determining levels of anesthesia. This is most likely to occur when greater than 0.05 mg/kg is given and when narcotic analgesics are used concomitantly with the recommended dose (see ADVERSE REACTIONS).

As with all benzodiazepines, paradoxical reactions may occur in rare instances and in an unpredictable fashion (see ADVERSE REACTIONS). In these instances, further use of the drug in these patients should be considered with caution.

There have been reports of possible propylene glycol toxicity (e.g., lactic acidosis, hyperosmolality, hypotension) and possible polyethylene glycol toxicity (e.g., acute tubular necrosis) during administration of Lorazepam Injection at higher than recommended doses. Symptoms may be more likely to develop in patients with renal impairment.

Information for Patients

RISKS FROM CONCOMITANT USE WITH OPIOIDS
Concomitant use of benzodiazepines, including Lorazepam Injection, and opioids may result in profound sedation, respiratory depression, coma, and death (see WARNINGS and PRECAUTIONS, Drug Interactions).
ABUSE, MISUSE, AND ADDICTION
Inform patients that the use of Lorazepam Injection more frequently than recommended, even at recommended dosages, exposes users to risks of abuse, misuse, and addiction, which can lead to overdose and death, especially when used in combination with other medications (e.g., opioid analgesics), alcohol, and/or illicit substances. Inform patients about the signs and symptoms of benzodiazepine abuse, misuse, and addiction; to seek medical help if they develop these signs and/or symptoms; and on the proper disposal of unused drug (see WARNINGS and DRUG ABUSE AND DEPENDENCE).
WITHDRAWAL REACTIONS
Inform patients that use of Lorazepam Injection more frequently than recommended may lead to clinically significant physical dependence and that abrupt discontinuation or rapid dosage reduction of Lorazepam Injection may precipitate acute withdrawal reactions, which can be life-threatening. Inform patients that in some cases, patients taking benzodiazepines have developed a protracted withdrawal syndrome with withdrawal symptoms lasting weeks to more than 12 months (see WARNINGS and DRUG ABUSE AND DEPENDENCE).
EXCESSIVE SEDATION
Patients should be informed of the pharmacological effects of the drug, including sedation, relief of anxiety, and lack of recall, the duration of these effects (about 8 hours), and be apprised of the risks as well as the benefits of therapy.

Patients who receive Lorazepam Injection as a premedicant should be cautioned that driving a motor vehicle, operating machinery, or engaging in hazardous or other activities requiring attention and coordination, should be delayed for 24 to 48 hours following the injection or until the effects of the drug, such as drowsiness, have subsided, whichever is longer. Sedatives, tranquilizers and narcotic analgesics may produce a more prolonged and profound effect when administered along with injectable lorazepam. This effect may take the form of excessive sleepiness or drowsiness and, on rare occasions, interfere with recall and recognition of events of the day of surgery and the day after.

Patients should be advised that getting out of bed unassisted may result in falling and injury if undertaken within 8 hours of receiving Lorazepam Injection. Since tolerance for CNS depressants will be diminished in the presence of Lorazepam Injection, these substances should either be avoided or taken in reduced dosage. Alcoholic beverages should not be consumed for at least 24 to 48 hours after receiving lorazepam injectable due to the additive effects on central-nervous-system depression seen with benzodiazepines in general. Elderly patients should be told that Lorazepam Injection may make them very sleepy for a period longer than 6 to 8 hours following surgery.

EFFECT OF ANESTHETIC AND SEDATION DRUGS ON EARLY BRAIN DEVELOPMENT
Studies conducted in young animals and children suggest repeated or prolonged use of general anesthetic or sedation drugs in children younger than 3 years may have negative effects on their developing brains. Discuss with parents and caregivers the benefits, risks, and timing and duration of surgery or procedures requiring anesthetic and sedation drugs (see WARNINGS, Pediatric Neurotoxicity).

Laboratory Tests

In clinical trials, no laboratory test abnormalities were identified with either single or multiple doses of Lorazepam Injection. These tests included: CBC, urinalysis, SGOT, SGPT, bilirubin, alkaline phosphatase, LDH, cholesterol, uric acid, BUN, glucose, calcium, phosphorus, and total proteins.

Drug Interactions

INTERACTION WITH BENZODIAZEPINES AND OTHER CNS DEPRESSANTS

The concomitant use of benzodiazepines and opioids increases the risk of respiratory depression because of actions at different receptor sites in the CNS that control respiration. Benzodiazepines interact at GABAA sites and opioids interact primarily at mu receptors. When benzodiazepines and opioids are combined, the potential for benzodiazepines to significantly worsen opioid-related respiratory depression exists. Monitor patients closely for respiratory depression and sedation.

Lorazepam Injection, like other injectable benzodiazepines, produces additive depression of the central nervous system when administered with other CNS depressants such as ethyl alcohol, phenothiazines, barbiturates, MAO inhibitors, and other antidepressants.

When scopolamine is used concomitantly with injectable lorazepam, an increased incidence of sedation, hallucinations and irrational behavior has been observed.

There have been rare reports of significant respiratory depression, stupor and/or hypotension with the concomitant use of loxapine and lorazepam.

Marked sedation, excessive salivation, ataxia, and, rarely, death have been reported with the concomitant use of clozapine and lorazepam.

Apnea, coma, bradycardia, arrhythmia, heart arrest, and death have been reported with the concomitant use of haloperidol and lorazepam.

The risk of using lorazepam in combination with scopolamine, loxapine, clozapine, haloperidol, or other CNS-depressant drugs has not been systematically evaluated. Therefore, caution is advised if the concomitant administration of lorazepam and these drugs is required.

Concurrent administration of any of the following drugs with lorazepam had no effect on the pharmacokinetics of lorazepam: metoprolol, cimetidine, ranitidine, disulfiram, propranolol, metronidazole, and propoxyphene. No change in lorazepam dosage is necessary when concomitantly given with any of these drugs.

LORAZEPAM-VALPROATE INTERACTION

Concurrent administration of lorazepam (2 mg intravenously) with valproate (250 mg twice daily orally for 3 days) to 6 healthy male subjects resulted in decreased total clearance of lorazepam by 40% and decreased formation rate of lorazepam glucuronide by 55%, as compared with lorazepam administered alone. Accordingly, lorazepam plasma concentrations were about two-fold higher for at least 12 hours post-dose administration during valproate treatment. Lorazepam dosage should be reduced to 50% of the normal adult dose when this drug combination is prescribed in patients (see DOSAGE AND ADMINISTRATION).

LORAZEPAM-ORAL CONTRACEPTIVE STEROIDS INTERACTION

Coadministration of lorazepam (2 mg intravenously) with oral contraceptive steroids (norethindrone acetate, 1 mg, and ethinyl estradiol, 50 μg, for at least 6 months) to healthy females (n=7) was associated with a 55% decrease in half-life, a 50% increase in the volume of distribution, thereby resulting in an almost 3.7-fold increase in total clearance of lorazepam as compared with control healthy females (n=8). It may be necessary to increase the dose of lorazepam in female patients who are concomitantly taking oral contraceptives (see DOSAGE AND ADMINISTRATION).

LORAZEPAM-PROBENECID INTERACTION

Concurrent administration of lorazepam (2 mg intravenously) with probenecid (500 mg orally every 6 hours) to 9 healthy volunteers resulted in a prolongation of lorazepam half-life by 130% and a decrease in its total clearance by 45%. No change in volume of distribution was noted during probenecid co-treatment. Lorazepam dosage needs to be reduced by 50% when coadministered with probenecid (see DOSAGE AND ADMINISTRATION).

Drug/Laboratory Test Interactions

No laboratory test abnormalities were identified when lorazepam was given alone or concomitantly with another drug, such as narcotic analgesics, inhalation anesthetics, scopolamine, atropine, and a variety of tranquilizing agents.

Carcinogenesis, Mutagenesis, Impairment of Fertility

No evidence of carcinogenic potential emerged in rats and mice during an 18-month study with oral lorazepam. No studies regarding mutagenesis have been performed. The results of a preimplantation study in rats, in which the oral lorazepam dose was 20 mg/kg, showed no impairment of fertility.

Pregnancy

Teratogenic Effects (see WARNINGS).

Published studies in pregnant primates demonstrate that the administration of anesthetic and sedation drugs that block NMDA receptors and/or potentiate GABA activity during the period of peak brain development increases neuronal apoptosis in the developing brain of the offspring when used for longer than 3 hours. There are no data on pregnancy exposures in primates corresponding to periods prior to the third trimester in humans.

In a published study in primates, administration of an anesthetic dose of ketamine for 24 hours on Gestation Day 122 increased neuronal apoptosis in the developing brain of the fetus. In other published studies, administration of either isoflurane or propofol for 5 hours on Gestation Day 120 resulted in increased neuronal and oligodendrocyte apoptosis in the developing brain of the offspring. With respect to brain development, this time period corresponds to the third trimester of gestation in the human. The clinical significance of these findings is not clear; however, studies in juvenile animals suggest neuroapoptosis correlates with long-term cognitive deficits (see WARNINGS, Pediatric Neurotoxicity, Pediatric Use, and ANIMAL TOXICOLOGY AND/OR PHARMACOLOGY).

Labor and Delivery

There are insufficient data to support the use of Lorazepam Injection during labor and delivery, including cesarean section; therefore, its use in this clinical circumstance is not recommended.

Nursing Mothers

Lorazepam has been detected in human breast milk. Therefore, lorazepam should not be administered to nursing mothers because, like other benzodiazepines, the possibility exists that lorazepam may sedate or otherwise adversely affect the infant.

Pediatric Use

STATUS EPILEPTICUS

The safety and effectiveness of lorazepam for status epilepticus have not been established in pediatric patients. A randomized, double-blind, superiority-design clinical trial of lorazepam versus intravenous diazepam in 273 pediatric patients ages 3 months to 17 years failed to establish the efficacy of lorazepam for the treatment of status epilepticus. In that trial, assisted ventilation was required in 18% of patients treated with lorazepam versus 16% of patients treated with diazepam. Patients treated with lorazepam were also more likely to be reported as sedated (67% for lorazepam vs. 50% for diazepam), and the time for return to baseline mental status was, on average, 2 hours longer for lorazepam than for diazepam.
Open-label studies described in the medical literature included 273 pediatric patients; the age range was from a few hours old to 18 years of age. Paradoxical excitation was observed in 10% to 30% of the pediatric patients under 8 years of age and was characterized by tremors, agitation, euphoria, logorrhea, and brief episodes of visual hallucinations. Paradoxical excitation in pediatric patients also has been reported with other benzodiazepines when used for status epilepticus, as an anesthesia, or for pre-chemotherapy treatment.

Pediatric patients (as well as adults) with atypical petit mal status epilepticus have developed brief tonic-clonic seizures shortly after lorazepam was given. This “paradoxical” effect was also reported for diazepam and clonazepam. Nevertheless, the development of seizures after treatment with benzodiazepines is probably rare, based on the incidence in the uncontrolled treatment series reported (i.e., seizures were not observed for 112 pediatric patients and 18 adults or during approximately 400 doses).

Lorazepam Injection contains benzyl alcohol as a preservative. Benzyl alcohol, a component of this product, has been associated with serious adverse events and death, particularly in pediatric patients. The “gasping syndrome”, (characterized by central nervous system depression, metabolic acidosis, gasping respirations, and high levels of benzyl alcohol and its metabolites found in the blood and urine) has been associated with benzyl alcohol dosages greater than 99 mg/kg/day in neonates and low-birth-weight neonates. Additional symptoms may include gradual neurological deterioration, seizures, intracranial hemorrhage, hematologic abnormalities, skin breakdown, hepatic and renal failure, hypotension, bradycardia, and cardiovascular collapse. Although normal therapeutic doses of this product deliver amounts of benzyl alcohol that are substantially lower than those reported in association with the “gasping syndrome”, the minimum amount of benzyl alcohol at which toxicity may occur is not known. Premature and low-birth-weight infants, as well as patients receiving high dosages, may be more likely to develop toxicity. Practitioners administering this and other medications containing benzyl alcohol should consider the combined daily metabolic load of benzyl alcohol from all sources.

PREANESTHETIC

There are insufficient data to support the efficacy of injectable lorazepam as a preanesthetic agent in patients less than 18 years of age.

GENERAL

Seizure activity and myoclonus have been reported to occur following administration of Lorazepam Injection, especially in very low birth weight neonates.

Pediatric patients may exhibit a sensitivity to benzyl alcohol, polyethylene glycol and propylene glycol, components of Lorazepam Injection (see CONTRAINDICATIONS). The “gasping syndrome”, characterized by central nervous system depression, metabolic acidosis, gasping respirations, and high levels of benzyl alcohol and its metabolites found in the blood and urine, has been associated with the administration of intravenous solutions containing the preservative benzyl alcohol in neonates. Additional symptoms may include gradual neurological deterioration, seizures, intracranial hemorrhage, hematologic abnormalities, skin breakdown, hepatic and renal failure, hypotension, bradycardia, and cardiovascular collapse. Central nervous system toxicity, including seizures and intraventricular hemorrhage, as well as unresponsiveness, tachypnea, tachycardia, and diaphoresis have been associated with propylene glycol toxicity. Although normal therapeutic doses of Lorazepam Injection contain very small amounts of these compounds, premature and low-birth-weight infants as well as pediatric patients receiving high doses may be more susceptible to their effects.

Published juvenile animal studies demonstrate that the administration of anesthetic and sedation drugs, such as lorazepam that either block NMDA receptors or potentiate the activity of GABA during the period of rapid brain growth or synaptogenesis, results in widespread neuronal and oligodendrocyte cell loss in the developing brain and alterations in synaptic morphology and neurogenesis. Based on comparisons across species, the window of vulnerability to these changes is believed to correlate with exposures in the third trimester of gestation through the first several months of life, but may extend out to approximately 3 years of age in humans.

In primates, exposure to 3 hours of ketamine that produced a light surgical plane of anesthesia did not increase neuronal cell loss, however, treatment regimens of 5 hours or longer of isoflurane increased neuronal cell loss. Data from isoflurane-treated rodents and ketamine-treated primates suggest that the neuronal and oligodendrocyte cell losses are associated with prolonged cognitive deficits in learning and memory. The clinical significance of these nonclinical findings is not known, and healthcare providers should balance the benefits of appropriate anesthesia in pregnant women, neonates and young children who require procedures with the potential risks suggested by the nonclinical data (see WARNINGS, Pediatric Neurotoxicity; PRECAUTIONS, Pregnancy; ANIMAL TOXICOLOGY AND/OR PHARMACOLOGY).

Geriatric Use

Clinical studies of lorazepam generally were not adequate to determine whether subjects aged 65 and over respond differently than younger subjects; however, age over 65 may be associated with a greater incidence of central nervous system depression and more respiratory depression (see WARNINGS, Preanesthetic Use, PRECAUTIONS, General and ADVERSE REACTIONS, Preanesthetic).

Age does not appear to have a clinically significant effect on lorazepam kinetics (see CLINICAL PHARMACOLOGY).

Clinical circumstances, some of which may be more common in the elderly, such as hepatic or renal impairment, should be considered. Greater sensitivity (e.g., sedation) of some older individuals cannot be ruled out. In general, dose selection for an elderly patient should be cautious, usually starting at the low end of the dosing range (see DOSAGE AND ADMINISTRATION).

ADVERSE REACTIONS

Status Epilepticus

The most important adverse clinical event caused by the use of Lorazepam Injection is respiratory depression (see WARNINGS).

The adverse clinical events most commonly observed with the use of Lorazepam Injection in clinical trials evaluating its use in status epilepticus were hypotension, somnolence, and respiratory failure.

INCIDENCE IN CONTROLLED CLINICAL TRIALS

All adverse events were recorded during the trials by the clinical investigators using terminology of their own choosing. Similar types of events were grouped into standardized categories using modified COSTART dictionary terminology. These categories are used in the table and listings below with the frequencies representing the proportion of individuals exposed to Lorazepam Injection or to comparative therapy.

The prescriber should be aware that these figures cannot be used to predict the frequency of adverse events in the course of usual medical practice where patient characteristics and other factors may differ from those prevailing during clinical studies. Similarly, the cited frequencies cannot be directly compared with figures obtained from other clinical investigators involving different treatment, uses, or investigators. An inspection of these frequencies, however, does provide the prescribing physician with one basis to estimate the relative contribution of drug and nondrug factors to the adverse event incidences in the population studied.

COMMONLY OBSERVED ADVERSE EVENTS IN A CONTROLLED DOSE-COMPARISON CLINICAL TRIAL

Table 1 lists the treatment-emergent adverse events that occurred in the patients treated with Lorazepam Injection in a dose-comparison trial of lorazepam 1 mg, 2 mg, and 4 mg.

TABLE 1. NUMBER (%) OF STUDY EVENTS IN A DOSE COMPARISON CLINICAL TRIAL
Body System Event | Lorazepam Injection (n=130) [One hundred and thirty (130) patients received Lorazepam Injection.]
Any Study Event (1 or more) [Totals are not necessarily the sum of the individual study events because a patient may report two or more different study events in the same body system.] | 16 (12.3%)
Body as a whole
Infection | 1 (<1%)
Cardiovascular system
Hypotension | 2 (1.5%)
Digestive system
Liver function tests abnormal | 1 (<1%)
Nausea | 1 (<1%)
Vomiting | 1 (<1%)
Metabolic and Nutritional
Acidosis | 1 (<1%)
Nervous system
Brain edema | 1 (<1%)
Coma | 1 (<1%)
Convulsion | 1 (<1%)
Somnolence | 2 (1.5%)
Thinking abnormal | 1 (<1%)
Respiratory system
Hyperventilation | 1 (<1%)
Hypoventilation | 1 (<1%)
Respiratory failure | 2 (1.5%)
Terms not classifiable
Injection site reaction | 1 (<1%)
Urogenital system
Cystitis | 1 (<1%)

COMMONLY OBSERVED ADVERSE EVENTS IN ACTIVE-CONTROLLED CLINICAL TRIALS

In two studies, patients who completed the course of treatment for status epilepticus were permitted to be reenrolled and to receive treatment for a second status episode, given that there was a sufficient interval between the two episodes. Safety was determined from all treatment episodes for all intent-to-treat patients, i.e., from all “patient-episodes.” Table 2 lists the treatment-emergent adverse events that occurred in at least 1% of the patient-episodes in which Lorazepam Injection or diazepam was given. The table represents the pooling of results from the two controlled trials.

TABLE 2. NUMBER (%) OF STUDY EVENTS IN ACTIVE CONTROLLED CLINICAL TRIAL
Body System Event | Lorazepam Injection (n=85) [The number indicates the number of “patient-episodes.” Patient-episodes were used rather than “patients” because a total of 7 patients were reenrolled for the treatment of a second episode of status: 5 patients received Lorazepam Injection on two occasions that were far enough apart to establish the diagnosis of status epilepticus for each episode, and, using the same time criterion, 2 patients received diazepam on two occasions.] | Diazepam (n=80)
Any Study Event (1 or more) [Totals are not necessarily the sum of the individual study events because a patient may report two or more different study events in the same body system.] | 14 (16.5%) | 11 (13.8%)
Body as a whole
Headache | 1 (1.2%) | 1 (1.3%)
Cardiovascular system
Hypotension | 2 (2.4%) | 0
Hemic and lymphatic system
Hypochromic anemia | 0 | 1 (1.3%)
Leukocytosis | 0 | 1 (1.3%)
Thrombocythemia | 0 | 1 (1.3%)
Nervous system
Coma | 1 (1.2 %) | 1 (1.3%)
Somnolence | 3 (3.5%) | 3 (3.8%)
Stupor | 1 (1.2%) | 0
Respiratory system
Hypoventilation | 1 (1.2%) | 2 (2.5%)
Apnea | 1 (1.2%) | 1 (1.3%)
Respiratory failure | 2 (2.4%) | 1 (1.3%)
Respiratory disorder | 1 (1.2%) | 0

These trials were not designed or intended to demonstrate the comparative safety of the two treatments.

The overall adverse experience profile for lorazepam was similar between women and men. There are insufficient data to support a statement regarding the distribution of adverse events by race. Generally, age greater than 65 years may be associated with a greater incidence of central-nervous-system depression and more respiratory depression.

OTHER EVENTS OBSERVED DURING THE PRE-MARKETING EVALUATION OF LORAZEPAM INJECTION FOR THE TREATMENT OF STATUS EPILEPTICUS

Lorazepam Injection, active comparators, and Lorazepam Injection in combination with a comparator were administered to 488 individuals during controlled and open-label clinical trials. Because of reenrollments, these 488 patients participated in a total of 521 patient-episodes. Lorazepam Injection alone was given in 69% of these patient-episodes (n=360). The safety information below is based on data available from 326 of these patient-episodes in which Lorazepam Injection was given alone.

All adverse events that were seen once are listed, except those already included in previous listings (Table 1 and Table 2).

Study events were classified by body system in descending frequency by using the following definitions: frequent adverse events were those that occurred in at least 1/100 individuals; infrequent study events were those that occurred in 1/100 to 1/1000 individuals.

Frequent and Infrequent Study Events

BODY AS A WHOLE - | Infrequent: asthenia, chills, headache, infection.
DIGESTIVE SYSTEM - | Infrequent: abnormal liver function test, increased salivation, nausea, vomiting.
METABOLIC AND NUTRITIONAL - | Infrequent: acidosis, alkaline phosphatase increased.
NERVOUS SYSTEM - | Infrequent: agitation, ataxia, brain edema, coma, confusion, convulsion, hallucinations, myoclonus, stupor, thinking abnormal, tremor.
RESPIRATORY SYSTEM - | Frequent: apnea; Infrequent: hyperventilation, hypoventilation, respiratory disorder.
TERMS NOT CLASSIFIABLE - | Infrequent: injection site reaction.
UROGENITAL SYSTEM- | Infrequent: cystitis.

Preanesthetic

CENTRAL NERVOUS SYSTEM

The most frequent adverse drug event reported with injectable lorazepam is central-nervous-system depression. The incidence varied from one study to another, depending on the dosage, route of administration, use of other central-nervous-system depressants, and the investigator’s opinion concerning the degree and duration of desired sedation. Excessive sleepiness and drowsiness were the most common consequences of CNS depression. This interfered with patient cooperation in approximately 6% (25/446) of patients undergoing regional anesthesia, causing difficulty in assessing levels of anesthesia. Patients over 50 years of age had a higher incidence of excessive sleepiness or drowsiness when compared with those under 50 (21/106 versus 24/245) when lorazepam was given intravenously (see DOSAGE AND ADMINISTRATION). On rare occasion (3/1580) the patient was unable to give personal identification in the operating room on arrival, and one patient fell when attempting premature ambulation in the postoperative period.

Symptoms such as restlessness, confusion, depression, crying, sobbing, and delirium occurred in about 1.3% (20/1580). One patient injured himself by picking at his incision during the immediate postoperative period.

Hallucinations were present in about 1% (14/1580) of patients and were visual and self-limiting.

An occasional patient complained of dizziness, diplopia and/or blurred vision. Depressed hearing was infrequently reported during the peak-effect period.

An occasional patient had a prolonged recovery room stay, either because of excessive sleepiness or because of some form of inappropriate behavior. The latter was seen most commonly when scopolamine was given concomitantly as a premedicant. Limited information derived from patients who were discharged the day after receiving injectable lorazepam showed one patient complained of some unsteadiness of gait and a reduced ability to perform complex mental functions. Enhanced sensitivity to alcoholic beverages has been reported more than 24 hours after receiving injectable lorazepam, similar to experience with other benzodiazepines.

LOCAL EFFECTS

Intramuscular injection of lorazepam has resulted in pain at the injection site, a sensation of burning, or observed redness in the same area in a very variable incidence from one study to another. The overall incidence of pain and burning in patients was about 17% (146/859) in the immediate postinjection period and about 1.4% (12/859) at the 24-hour observation time. Reactions at the injection site (redness) occurred in approximately 2% (17/859) in the immediate postinjection period and were present 24 hours later in about 0.8% (7/859).

Intravenous administration of lorazepam resulted in painful responses in 13/771 patients or approximately 1.6% in the immediate postinjection period, and 24 hours later 4/771 patients or about 0.5% still complained of pain. Redness did not occur immediately following intravenous injection but was noted in 19/771 patients at the 24-hour observation period. This incidence is similar to that observed with an intravenous infusion before lorazepam is given. Intra-arterial injection may produce arteriospasm resulting in gangrene which may require amputation (see CONTRAINDICATIONS).

CARDIOVASCULAR SYSTEM

Hypertension (0.1%) and hypotension (0.1%) have occasionally been observed after patients have received injectable lorazepam.

RESPIRATORY SYSTEM

Five patients (5/446) who underwent regional anesthesia were observed to have airway obstruction. This was believed due to excessive sleepiness at the time of the procedure and resulted in temporary hypoventilation. In this instance, appropriate airway management may become necessary (see CLINICAL PHARMACOLOGY, WARNINGS, and PRECAUTIONS).

OTHER ADVERSE EXPERIENCES

Skin rash, nausea and vomiting have occasionally been noted in patients who have received injectable lorazepam combined with other drugs during anesthesia and surgery.

Paradoxical Reactions

As with all benzodiazepines, paradoxical reactions such as stimulation, mania, irritability, restlessness, agitation, aggression, psychosis, hostility, rage, or hallucinations may occur in rare instances and in an unpredictable fashion. In these instances, further use of the drug in these patients should be considered with caution (see PRECAUTIONS, General).

Postmarketing Reports

Voluntary reports of other adverse events temporally associated with the use of Lorazepam Injection that have been received since market introduction and that may have no causal relationship with the use of Lorazepam Injection include the following: acute brain syndrome, aggravation of pheochromocytoma, amnesia, apnea/respiratory arrest, arrhythmia, bradycardia, brain edema, coagulation disorder, coma, convulsion, gastrointestinal hemorrhage, heart arrest/failure, heart block, liver damage, lung edema, lung hemorrhage, nervousness, neuroleptic malignant syndrome, paralysis, pericardial effusion, pneumothorax, pulmonary hypertension, tachycardia, thrombocytopenia, urinary incontinence, ventricular arrhythmia.

Fatalities also have been reported, usually in patients on concomitant medications (e.g., respiratory depressants) and/or with other medical conditions (e.g., obstructive sleep apnea).

DRUG ABUSE AND DEPENDENCE

Controlled Substance

Lorazepam Injection is a Schedule IV controlled substance.

Abuse

Lorazepam Injection is a benzodiazepine and a CNS depressant with a potential for abuse and addiction. Abuse is the intentional, non-therapeutic use of a drug, even once, for its desirable psychological or physiological effects. Misuse is the intentional use, for therapeutic purposes, of a drug by an individual in a way other than prescribed by a health care provider or for whom it was not prescribed. Drug addiction is a cluster of behavioral, cognitive, and physiological phenomena that may include a strong desire to take the drug, difficulties in controlling drug use (e.g., continuing drug use despite harmful consequences, giving a higher priority to drug use than other activities and obligations), and possible tolerance or physical dependence. Even taking benzodiazepines as prescribed may put patients at risk for abuse and misuse of their medication. Abuse and misuse of benzodiazepines may lead to addiction.
Abuse and misuse of benzodiazepines often (but not always) involve the use of doses greater than the maximum recommended dosage and commonly involve concomitant use of other medications, alcohol, and/or illicit substances, which is associated with an increased frequency of serious adverse outcomes, including respiratory depression, overdose, or death. Benzodiazepines are often sought by individuals who abuse drugs and other substances, and by individuals with addictive disorders (see WARNINGS, Abuse, Misuse, and Addiction).
The following adverse reactions have occurred with benzodiazepine abuse and/or misuse: abdominal pain, amnesia, anorexia, anxiety, aggression, ataxia, blurred vision, confusion, depression, disinhibition, disorientation, dizziness, euphoria, impaired concentration and memory, indigestion, irritability, muscle pain, slurred speech, tremors, and vertigo.
The following severe adverse reactions have occurred with benzodiazepine abuse and/or misuse: delirium, paranoia, suicidal ideation and behavior, seizures, coma, breathing difficulty, and death. Death is more often associated with polysubstance use (especially benzodiazepines with other CNS depressants such as opioids and alcohol).

Dependence

PHYSICAL DEPENDENCE AFTER USE OF LORAZEPAM INJECTION MORE FREQUENTLY THAN RECOMMENDED
Lorazepam Injection may produce physical dependence if used more frequently than recommended. Physical dependence is a state that develops as a result of physiological adaptation in response to repeated drug use, manifested by withdrawal signs and symptoms after abrupt discontinuation or a significant dose reduction of a drug. Although Lorazepam Injection is indicated only for intermittent use (see INDICATIONS AND USAGE and DOSAGE AND ADMINISTRATION), if used more frequently than recommended, abrupt discontinuation or rapid dosage reduction or administration of flumazenil, a benzodiazepine antagonist, may precipitate acute withdrawal reactions, including seizures, which can be life-threatening.
Patients at an increased risk of withdrawal adverse reactions after benzodiazepine discontinuation or rapid dosage reduction include those who take higher dosages (i.e., higher and/or more frequent doses) and those who have had longer durations of use (see WARNINGS, Dependence and Withdrawal Reactions).
For patients using Lorazepam Injection more frequently than recommended, to reduce the risk of withdrawal reactions, use a gradual taper to discontinue Lorazepam Injection (see WARNINGS, Dependence and Withdrawal Reactions).

Acute Withdrawal Signs and Symptoms
Acute withdrawal signs and symptoms associated with benzodiazepines have included abnormal involuntary movements, anxiety, blurred vision, depersonalization, depression, derealization, dizziness, fatigue, gastrointestinal adverse reactions (e.g., nausea, vomiting, diarrhea, weight loss, decreased appetite), headache, hyperacusis, hypertension, irritability, insomnia, memory impairment, muscle pain and stiffness, panic attacks, photophobia, restlessness, tachycardia, and tremor. More severe acute withdrawal signs and symptoms, including life-threatening reactions, have included catatonia, convulsions, delirium tremens, depression, hallucinations, mania, psychosis, seizures, and suicidality.

Protracted Withdrawal Syndrome
Protracted withdrawal syndrome associated with benzodiazepines is characterized by anxiety, cognitive impairment, depression, insomnia, formication, motor symptoms (e.g., weakness, tremor, muscle twitches), paresthesia, and tinnitus that persists beyond 4 to 6 weeks after initial benzodiazepine withdrawal. Protracted withdrawal symptoms may last weeks to more than 12 months. As a result, there may be difficulty in differentiating withdrawal symptoms from potential re-emergence or continuation of symptoms for which the benzodiazepine was being used.

TOLERANCE
Tolerance to Lorazepam Injection may develop after use more frequently than recommended. Tolerance is a physiological state characterized by a reduced response to a drug after repeated administration (i.e., a higher dose of a drug is required to produce the same effect that was once obtained at a lower dose). Tolerance to the therapeutic effect of benzodiazepines may develop; however, little tolerance develops to the amnestic reactions and other cognitive impairments caused by benzodiazepines.

OVERDOSAGE

Symptoms

Overdosage of benzodiazepines is usually manifested by varying degrees of central-nervous-system depression, ranging from drowsiness to coma. In mild cases symptoms include drowsiness, mental confusion and lethargy. In more serious examples, symptoms may include ataxia, hypotonia, hypotension, hypnosis, stages one (1) to three (3) coma, and, very rarely, death.

Treatment

Treatment of overdosage is mainly supportive until the drug is eliminated from the body. Vital signs and fluid balance should be carefully monitored in conjunction with close observation of the patient. An adequate airway should be maintained and assisted respiration used as needed. With normally functioning kidneys, forced diuresis with intravenous fluids and electrolytes may accelerate elimination of benzodiazepines from the body. In addition, osmotic diuretics, such as mannitol, may be effective as adjunctive measures. In more critical situations, renal dialysis and exchange blood transfusions may be indicated. Lorazepam does not appear to be removed in significant quantities by dialysis, although lorazepam glucuronide may be highly dialyzable. The value of dialysis has not been adequately determined for lorazepam.

The benzodiazepine antagonist flumazenil may be used in hospitalized patients as an adjunct to, not as a substitute for, proper management of benzodiazepine overdose. The prescriber should be aware of a risk of seizure in association with flumazenil treatment, particularly in long-term benzodiazepine users and in cyclic antidepressant overdose. The complete flumazenil package insert including CONTRAINDICATIONS, WARNINGS and PRECAUTIONS should be consulted prior to use.

DOSAGE AND ADMINISTRATION

NOTE: CONTAINS BENZYL ALCOHOL (see WARNINGS and PRECAUTIONS, Pediatric Use).

Lorazepam must never be used without individualization of dosage particularly when used with other medications capable of producing central-nervous-system depression.

EQUIPMENT NECESSARY TO MAINTAIN A PATENT AIRWAY SHOULD BE IMMEDIATELY AVAILABLE PRIOR TO INTRAVENOUS ADMINISTRATION OF LORAZEPAM (see WARNINGS).

Status Epilepticus

GENERAL ADVICE

Status epilepticus is a potentially life-threatening condition associated with a high risk of permanent neurological impairment, if inadequately treated. The treatment of status, however, requires far more than the administration of an anticonvulsant agent. It involves observation and management of all parameters critical to maintaining vital function and the capacity to provide support of those functions as required. Ventilatory support must be readily available. The use of benzodiazepines, like Lorazepam Injection, is ordinarily only an initial step of a complex and sustained intervention which may require additional interventions, (e.g., concomitant intravenous administration of phenytoin). Because status epilepticus may result from a correctable acute cause such as hypoglycemia, hyponatremia, or other metabolic or toxic derangement, such an abnormality must be immediately sought and corrected. Furthermore, patients who are susceptible to further seizure episodes should receive adequate maintenance antiepileptic therapy.

Any healthcare professional who intends to treat a patient with status epilepticus should be familiar with this package insert and the pertinent medical literature concerning current concepts for the treatment of status epilepticus. A comprehensive review of the considerations critical to the informed and prudent management of status epilepticus cannot be provided in drug product labeling. The archival medical literature contains many informative references on the management of status epilepticus, among them the report of the working group on status epilepticus of the Epilepsy Foundation of America “Treatment of Convulsive Status Epilepticus” (JAMA 1993; 270:854-859). As noted in the report just cited, it may be useful to consult with a neurologist if a patient fails to respond (e.g., fails to regain consciousness).

INTRAVENOUS INJECTION

For the treatment of status epilepticus, the usual recommended dose of Lorazepam Injection is 4 mg given slowly (2 mg/min) for patients 18 years and older. If seizures cease, no additional Lorazepam Injection is required. If seizures continue or recur after a 10- to 15-minute observation period, an additional 4 mg intravenous dose may be slowly administered. Experience with further doses of lorazepam is very limited. The usual precautions in treating status epilepticus should be employed. An intravenous infusion should be started, vital signs should be monitored, an unobstructed airway should be maintained, and artificial ventilation equipment should be available.

INTRAMUSCULAR INJECTION

IM lorazepam is not preferred in the treatment of status epilepticus because therapeutic lorazepam levels may not be reached as quickly as with IV administration. However, when an intravenous port is not available, the IM route may prove useful (see CLINICAL PHARMACOLOGY, Pharmacokinetics and Metabolism).

PEDIATRIC

The safety of lorazepam in pediatric patients has not been established.

Preanesthetic

INTRAMUSCULAR INJECTION

For the designated indications as a premedicant, the usual recommended dose of lorazepam for intramuscular injection is 0.05 mg/kg up to a maximum of 4 mg. As with all premedicant drugs, the dose should be individualized (see CLINICAL PHARMACOLOGY, WARNINGS, PRECAUTIONS, and ADVERSE REACTIONS). Doses of other central-nervous-system-depressant drugs ordinarily should be reduced (see PRECAUTIONS). For optimum effect, measured as lack of recall, intramuscular lorazepam should be administered at least 2 hours before the anticipated operative procedure. Narcotic analgesics should be administered at their usual preoperative time.

There are insufficient data to support efficacy or make dosage recommendations for intramuscular lorazepam in patients less than 18 years of age; therefore, such use is not recommended.

INTRAVENOUS INJECTION

For the primary purpose of sedation and relief of anxiety, the usual recommended initial dose of lorazepam for intravenous injection is 2 mg total, or 0.02 mg/lb (0.044 mg/kg), whichever is smaller. This dose will suffice for sedating most adult patients and ordinarily should not be exceeded in patients over 50 years of age. In those patients in whom a greater likelihood of lack of recall for perioperative events would be beneficial, larger doses as high as 0.05 mg/kg up to a total of 4 mg may be administered (see CLINICAL PHARMACOLOGY, WARNINGS, PRECAUTIONS, and ADVERSE REACTIONS). Doses of other injectable central-nervous-system-depressant drugs ordinarily should be reduced (see PRECAUTIONS). For optimum effect, measured as lack of recall, intravenous lorazepam should be administered 15 to 20 minutes before the anticipated operative procedure.

There are insufficient data to support efficacy or make dosage recommendations for intravenous lorazepam in patients less than 18 years of age; therefore, such use is not recommended.

Dose Administration in Special Populations

ELDERLY PATIENTS AND PATIENTS WITH HEPATIC DISEASE

No dosage adjustments are needed in elderly patients and in patients with hepatic disease.

PATIENTS WITH RENAL DISEASE

For acute dose administration, adjustment is not needed for patients with renal disease. However, in patients with renal disease, caution should be exercised if frequent doses are given over relatively short periods of time (see CLINICAL PHARMACOLOGY).

DOSE ADJUSTMENT DUE TO DRUG INTERACTIONS

The dose of lorazepam should be reduced by 50% when coadministered with probenecid or valproate (see PRECAUTIONS, Drug Interactions).

It may be necessary to increase the dose of lorazepam in female patients who are concomitantly taking oral contraceptives.

Administration

When given intramuscularly, Lorazepam Injection, undiluted, should be injected deep in the muscle mass.

Injectable lorazepam can be used with atropine sulfate, narcotic analgesics, other parenterally used analgesics, commonly used anesthetics, and muscle relaxants.

Immediately prior to intravenous use, Lorazepam Injection must be diluted with an equal volume of compatible solution. Contents should be mixed thoroughly by gently inverting the container repeatedly until a homogenous solution results. Do not shake vigorously, as this will result in air entrapment. When properly diluted, the drug may be injected directly into a vein or into the tubing of an existing intravenous infusion. The rate of injection should not exceed 2.0 mg per minute.

Parenteral drug products should be inspected visually for particulate matter and discoloration prior to administration, whenever solution and container permit. Do not use if solution is discolored or contains a precipitate.

Lorazepam Injection is compatible for dilution purposes with the following solutions: Sterile Water for Injection, USP; Sodium Chloride Injection, USP; 5% Dextrose Injection, USP.

HOW SUPPLIED

Lorazepam Injection, USP is available in the following dosage strengths in single-dose and multiple-dose vials:

2 mg per mL, NDC 0641-6048-25, 25 x 1 mL vial
NDC 0641-6050-10, 10 x 10 mL vial
4 mg per mL, NDC 0641-6049-25, 25 x 1 mL vial
NDC 0641-6051-10, 10 x 10 mL vial

For IM or IV injection.
Store in a refrigerator.
PROTECT FROM LIGHT.
Use carton to protect contents from light.

ANIMAL TOXICOLOGY AND/OR PHARMACOLOGY

Published studies in animals demonstrate that the use of anesthetic agents during the period of rapid brain growth or synaptogenesis results in widespread neuronal and oligodendrocyte cell loss in the developing brain and alterations in synaptic morphology and neurogenesis. Based on comparisons across species, the window of vulnerability to these changes is believed to correlate with exposures in the third trimester through the first several months of life, but may extend out to approximately 3 years of age in humans.

In primates, exposure to 3 hours of an anesthetic regimen that produced a light surgical plane of anesthesia did not increase neuronal cell loss, however, treatment regimens of 5 hours or longer increased neuronal cell loss. Data in rodents and in primates suggest that the neuronal and oligodendrocyte cell losses are associated with subtle but prolonged cognitive deficits in learning and memory. The clinical significance of these nonclinical findings is not known, and healthcare providers should balance the benefits of appropriate anesthesia in neonates and young children who require procedures against the potential risks suggested by the nonclinical data (see WARNINGS, Pediatric Neurotoxicity; PRECAUTIONS, Pregnancy, Pediatric Use).

To report SUSPECTED ADVERSE REACTIONS, contact Hikma Pharmaceuticals USA Inc. at 1-877-845-0689, or the FDA at 1-800-FDA-1088 or www.fda.gov/medwatch.

For Product Inquiry call 1-877-845-0689.

Manufactured by:
Hikma Pharmaceuticals USA Inc.
Berkeley Heights, NJ 07922

Novaplus is a registered trademark of Vizient, Inc.

Revised March 2021 462-380-06

PRINCIPAL DISPLAY PANEL

NDC 0641-6048-01
Lorazepam CIV
Injection, USP
For IM use
Dilute for IV use
2 mg/mL
Protect from light
Refrigerate
1 mL Vial Rx ONLY

NDC 0641-6048-25 Rx ONLY
Lorazepam CIV
Injection, USP
For Intramuscular use
For Intravenous use, dilution
required; see insert.
2 mg/mL
Refrigerate
25 x 1 mL Vials

PRINCIPAL DISPLAY PANEL

NDC 0641-6050-01 Rx ONLY
Lorazepam
Injection, USP CIV
For Intramuscular use
For Intravenous use, dilution
required; see insert.
20 mg per 10 mL (2 mg/mL)
10 mL Multiple Dose Vial

NDC 0641-6050-10 Rx ONLY
Lorazepam
Injection, USP CIV
For Intramuscular use
For Intravenous use, dilution
required; see insert.
20 mg per 10 mL (2 mg/mL)
10 x 10 mL Multiple Dose Vials

PRINCIPAL DISPLAY PANEL

NDC 0641-6049-01
Lorazepam CIV
Injection, USP
For IM use
Dilute for IV use
4 mg/mL
Protect from light
Refrigerate
1 mL Vial Rx ONLY

NDC 0641-6049-25 Rx ONLY
Lorazepam
Injection, USP CIV
For Intramuscular use
For Intravenous use, dilution
required; see insert.
4 mg/mL
Refrigerate
25 x 1 mL Vials

PRINCIPAL DISPLAY PANEL

NDC 0641-6051-01 Rx ONLY
Lorazepam
Injection, USP CIV
For Intramuscular use
For Intravenous use, dilution
required; see insert.
40 mg per 10 mL (4 mg/mL)
10 mL Multiple Dose Vial

NDC 0641-6051-10 Rx ONLY
Lorazepam
Injection, USP CIV
For Intramuscular use
For Intravenous use, dilution
required; see insert.
40 mg per 10 mL (4 mg/mL)
10 x 10 mL Multiple Dose Vials